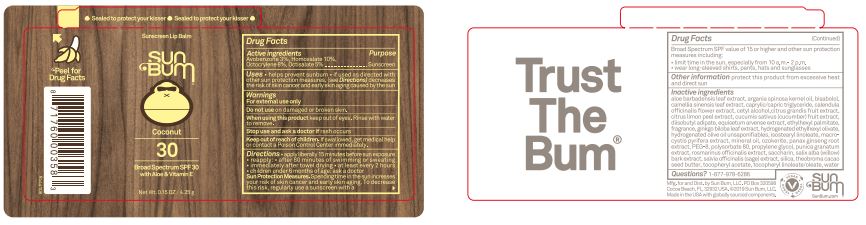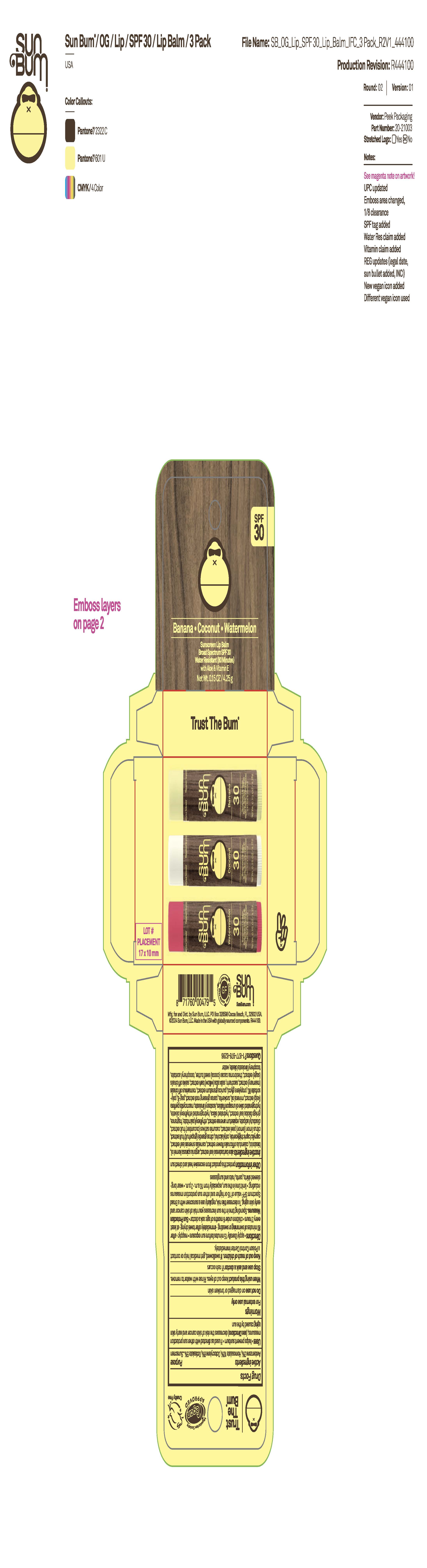 DRUG LABEL: Sun Bum Sunscreen Lip Balms Broad Spectrum SPF 30 - Banana, Coconut, Watermelon
NDC: 69039-827 | Form: STICK
Manufacturer: Sun Bum, LLC
Category: otc | Type: HUMAN OTC DRUG LABEL
Date: 20250825

ACTIVE INGREDIENTS: AVOBENZONE 30 mg/1 g; OCTISALATE 50 mg/1 g; HOMOSALATE 100 mg/1 g; OCTOCRYLENE 80 mg/1 g
INACTIVE INGREDIENTS: HYDROGENATED OLIVE OIL UNSAPONIFIABLES; MACROCYSTIS PYRIFERA (KELP); MINERAL OIL; CAPRYLIC/CAPRIC TRIGLYCERIDE; GRAPEFRUIT; CERESIN; PANAX GINSENG ROOT; WILLOW BARK; SAGE; .ALPHA.-TOCOPHEROL LINOLEATE, D-; DIISOBUTYL ADIPATE; HYDROGENATED ETHYLHEXYL OLIVATE; PUNICA GRANATUM WHOLE; SILICA; EQUISETUM ARVENSE WHOLE; PROPYLENE GLYCOL; SACCHARIN; BISABOLOL; THEOBROMA CACAO (COCOA) SEED BUTTER; PEG-8; POLYSORBATE 80; ROSMARINUS OFFICINALIS WHOLE; .ALPHA.-TOCOPHEROL ACETATE; CUCUMIS SATIVUS (CUCUMBER) FRUIT; CALENDULA OFFICINALIS FLOWER; WATER; CAMELLIA SINENSIS LEAF; CETYL ALCOHOL; ALOE BARBADENSIS LEAF; ARGANIA SPINOSA KERNEL OIL; LEMON PEEL; ETHYLHEXYL PALMITATE; GINKGO BILOBA LEAF; ISOSTEARYL LINOLEATE

Sun Bum Sunscreen Lip Balm Broad Spectrum SPF 30 - Coconut; Muti Pack - Banana, Coconut, Watermelon

Active Ingredients

Avobenzone 3%, Homosalate 10%, Octisalate 5%, Octocrylene 8%

Purpose

Sunscreen

Uses

• helps prevent sunburn • if used as directed with other sun protection measures, (see Directions) decreases the risk of skin cancer and early skin aging caused by the sun

Warnings

For external use only.

Do not use on damaged or broken skin

When using this product keep out of eyes. Rinse with water to remove.

Stop use and ask a doctor if rash occurs

Keep out of reach of children. If swallowed, get medical help or contact a Poison Control Center immediately.

Warnings

Keep Out Of Reach Of Children

Directions

• apply liberally 15 minutes before sun exposure

• reapply: • after 80 minutes of swimming or sweating • immediately after towel drying • at least every 2 hours

• children under 6 months of age: ask a doctor

• Sun Protection Measures. Spending time in the sun increases your risk of skin cancer and early skin aging. To decrease this risk, regularly use a sunscreen with a Broad Spectrum SPF value of 15 or higher and other sun protection measures including:

• limit time in the sun, especially from 10 a.m.- 2 p.m.

• wear long-sleeved shirts, pants, hats and sunglasses

Directions

• apply liberally 15 minutes before sun exposure

Other Information

protect this product from excessive heat and direct sun

Inactive Ingredients

aloe barbadensis leaf extract, argania spinosa kernel oil, bisabolol, camellia sinensis leaf extract, caprylic/capric triglyceride, calendula officinalis flower extract, cetyl alcohol, citrus grandis fruit extract, citrus limon peel extract, cucumis sativus (cucumber) fruit extract, diisobutyl adipate, equisetum arvense extract, ethylhexyl palmitate, fragrance, ginkgo biloba leaf extract, hydrogenated ethylhexyl olivate, hydrogenated olive oil unsaponifiables, isostearyl linoleate, macrocystis pyrifera extract, mineral oil, ozokerite, panax ginseng root extract, PEG-8, polysorbate 80, propylene glycol, punica granatum extract, rosmarinus officinalis extract, saccharin, salix alba (willow) bark extract, salvia officinalis (sage) extract, silica, theobroma cacao seed butter, tocopheryl acetate, tocopheryl linoleate/oleate, water

Questions?

1-877-978-6286